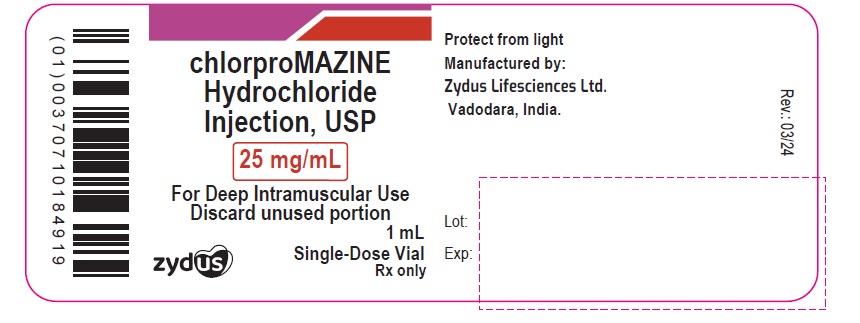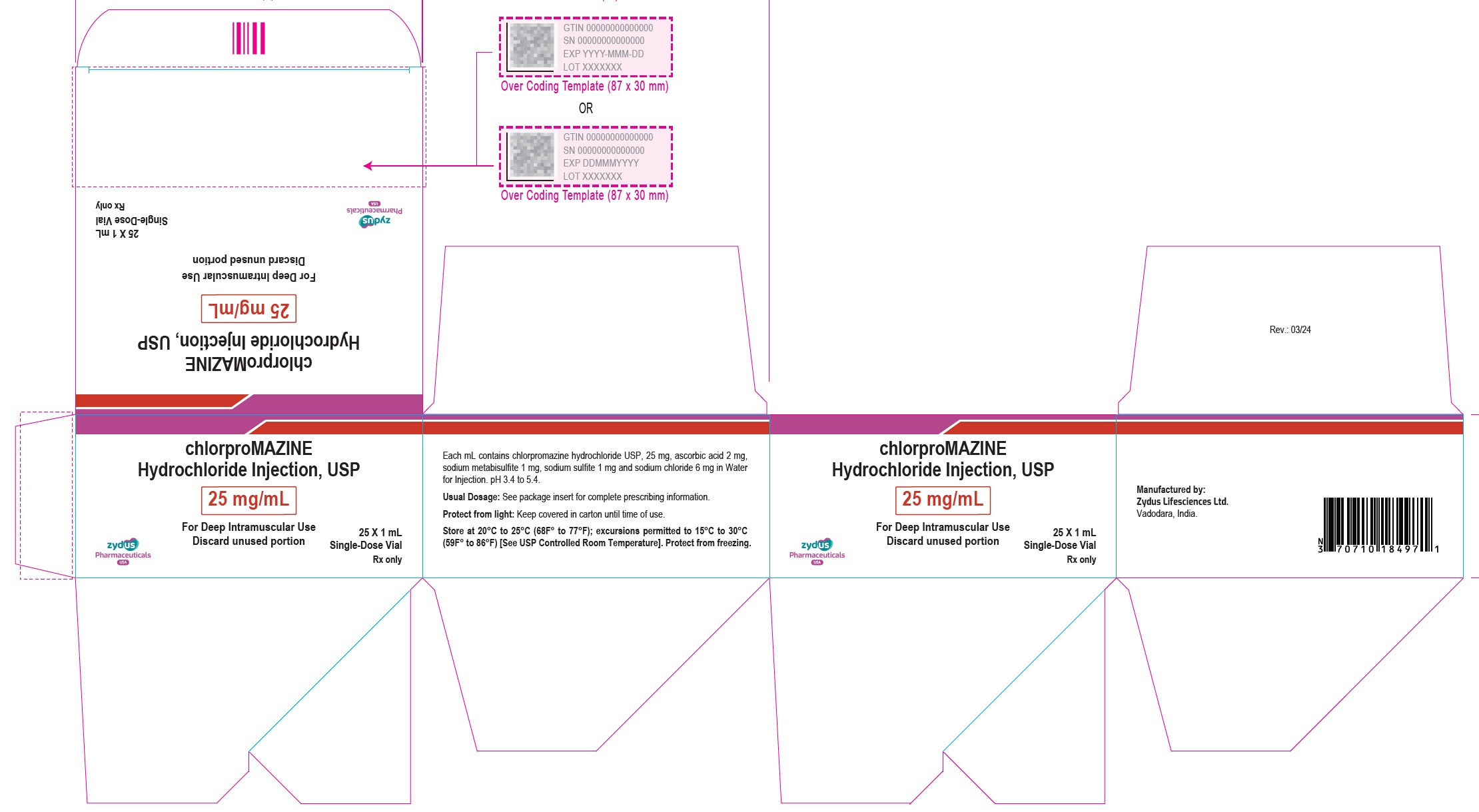 DRUG LABEL: Chlorpromazine Hydrochloride
NDC: 70771-1779 | Form: INJECTION
Manufacturer: Zydus Lifesciences Limited
Category: prescription | Type: HUMAN PRESCRIPTION DRUG LABEL
Date: 20251104

ACTIVE INGREDIENTS: CHLORPROMAZINE HYDROCHLORIDE 25 mg/1 mL
INACTIVE INGREDIENTS: ASCORBIC ACID 2 mg/1 mL; SODIUM METABISULFITE 1 mg/1 mL; SODIUM SULFITE 1 mg/1 mL; SODIUM CHLORIDE 6 mg/1 mL; WATER

Chlorpromazine Hydrochloride Injection, USP

PACKAGE LABEL.PRINCIPAL DISPLAY PANEL

NDC 70771-1778-1

chlorproMAZINE Hydrochloride Injection, USP

25 mg/mL

For Deep Intramuscular Use

Discard unused portion

1 mL Single-Dose Vial

Rx only

NDC 70771-1778-7

chlorproMAZINE Hydrochloride Injection, USP

25 mg/mL

For Deep Intramuscular Use

Discard unused portion

25 x 1 mL Single-Dose Vial

Rx only